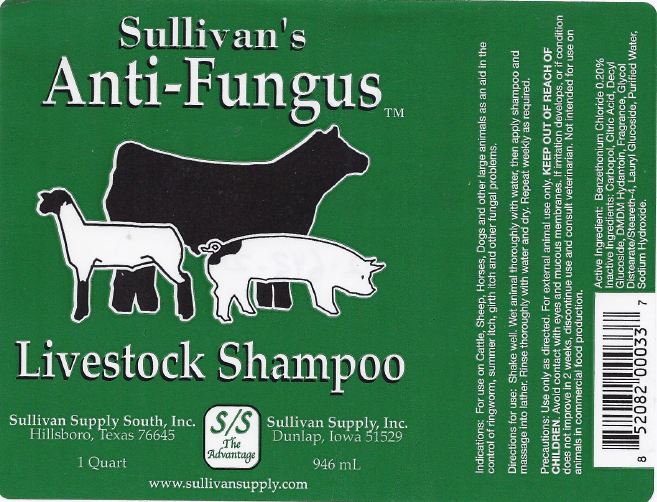 DRUG LABEL: Anti-Fungus
NDC: 42417-029 | Form: SHAMPOO
Manufacturer: Sullivan Supply, Inc.
Category: animal | Type: OTC ANIMAL DRUG LABEL
Date: 20120615

ACTIVE INGREDIENTS: BENZETHONIUM CHLORIDE 2.000 g/1.0 L

Anti-Fungus

Indications:

For use on Cattle, Sheep, Horses, Dogs and other large animals as an aid in the control of ringworm, summer itch, girth itch and other fungal problems.

Directions for Use:

Shake well. Wet animal thoroughly with water, then apply shampoo and massage into lather. Rinse thoroughly with water and dry. Repeat weekly as required.

Precautions:

Use only as directed. For animal external use only. Avoid contact with eyes or mucous membranes. If irritation develops, or if condition does not improve in 2 weeks, discontinue use and consult veterinarian. Not intended for use on animals in commercial food production.

Active Ingredient:

Benzethonium Chloride 0.20%

Inactive Ingredients:

Carbopol, Citric Acid, Decyl Glucoside, DMDM Hydantoin, Fragrance, Glycol Distearate/Steareth-4, Lauryl Glucoside, Purified Water, Sodium Hydroxide

Package Label

1 Quart Label

1 Quart Label

Distributed By

Sullivan Supply South, Inc.

Hillsboro, Texas 76645

Sullivan Supply, Inc.

Dunlap, Iowa 51529

www.sullivansupply.com